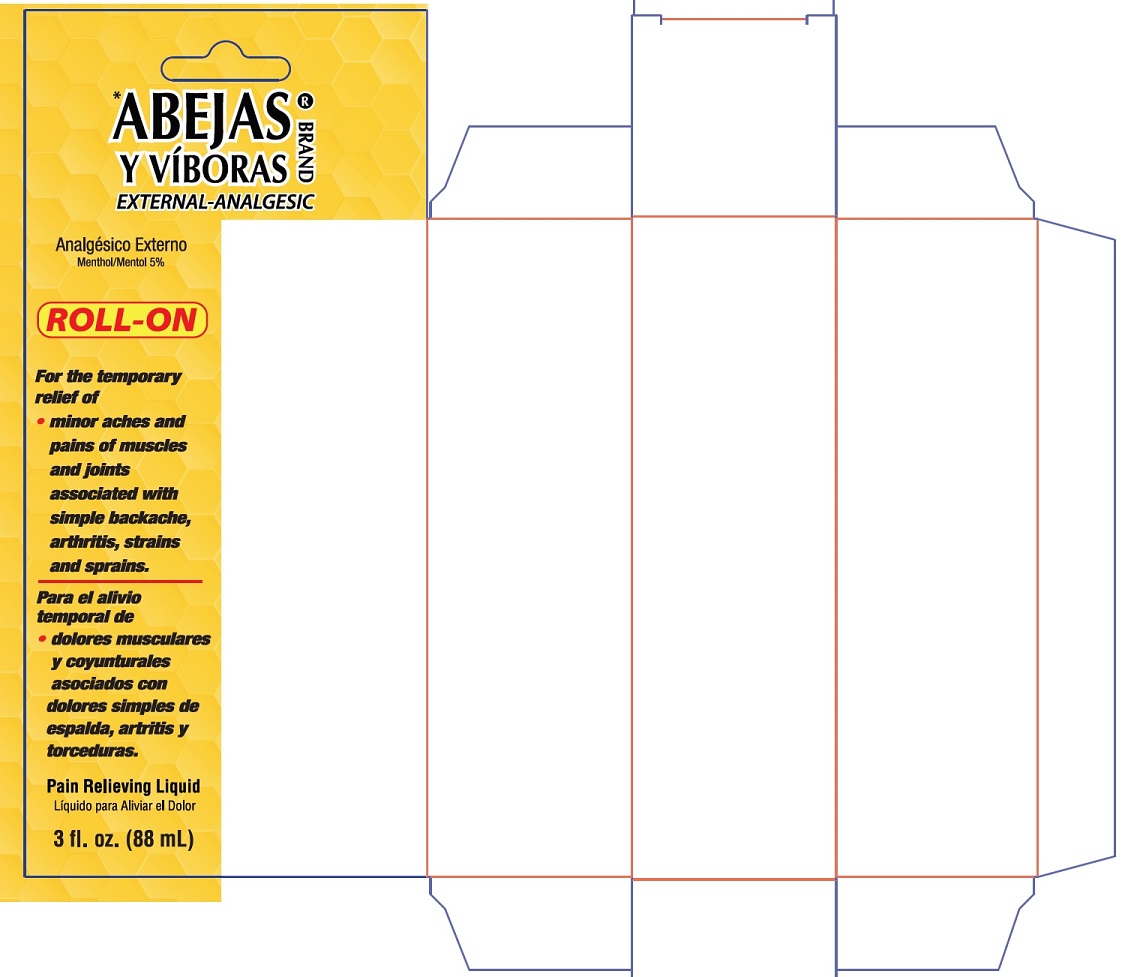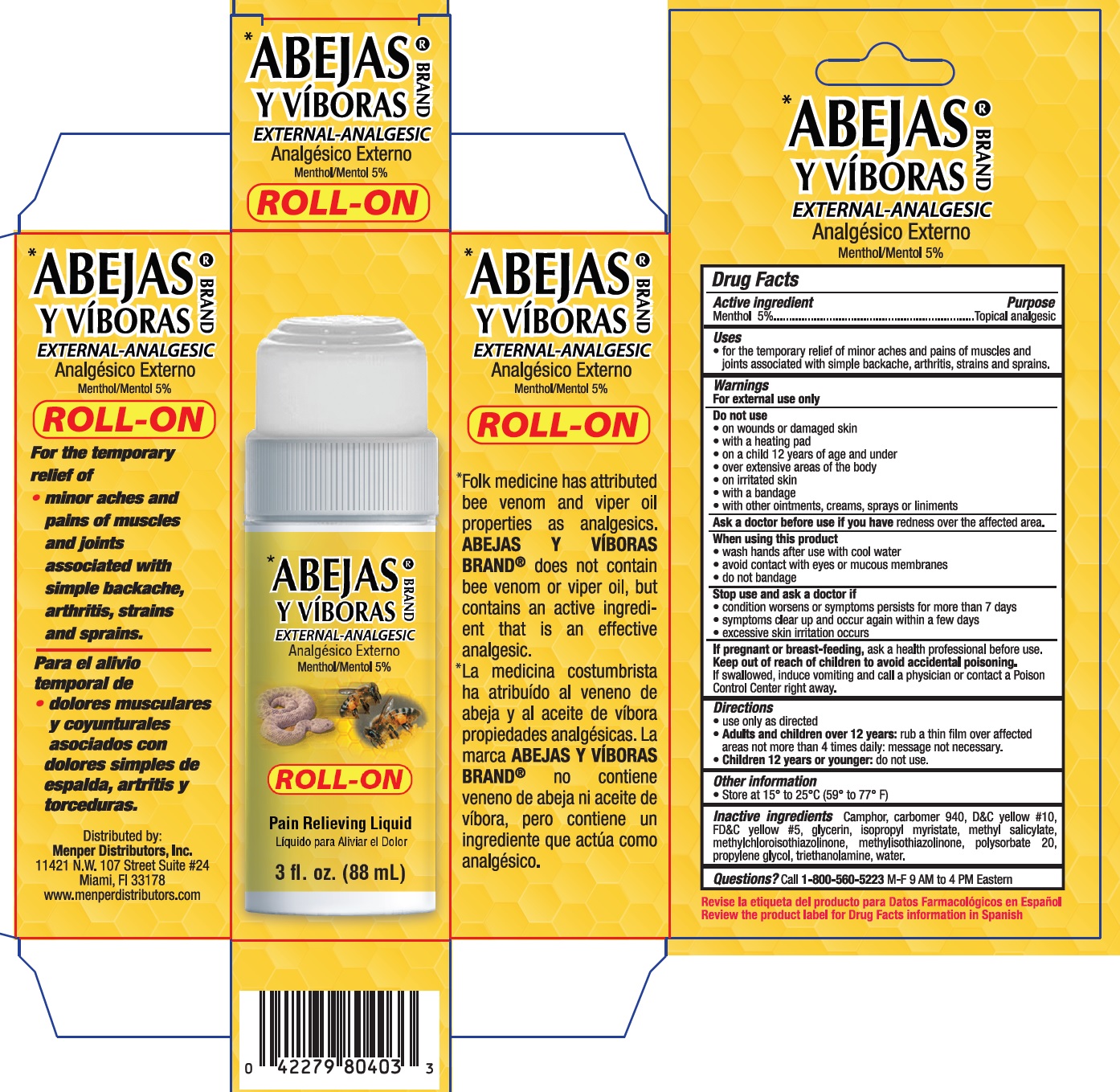 DRUG LABEL: Abejas y Viboras Brand Roll-On
NDC: 53145-703 | Form: GEL
Manufacturer: MENPER DISTRIBUTORS INC.
Category: otc | Type: HUMAN OTC DRUG LABEL
Date: 20210301

ACTIVE INGREDIENTS: MENTHOL 5 mg/100 mL
INACTIVE INGREDIENTS: CAMPHOR (SYNTHETIC); CARBOMER 940; D&C YELLOW NO. 10; FD&C YELLOW NO. 5; GLYCERIN; ISOPROPYL MYRISTATE; METHYL SALICYLATE; METHYLCHLOROISOTHIAZOLINONE; METHYLISOTHIAZOLINONE; POLYSORBATE 20; PROPYLENE GLYCOL; TROLAMINE; WATER

Active Ingredient

Menthol 5%

Purpose

Topical Analgesic

Uses

- for the temporary relief of minor aches and pains of muscles and joints associated with simple backache, arthristis, strains and sprains.

Warnings

For external use only

Do not use

- on wounds or damaged skin
- with a heating pad
- on a child 12 years of age and under
- over extensive areas of the body
- on irritated skin
- with a bandage
- with other ointments, creams, sprays or liniments

Ask a doctor before use if you have redness over the affected area.

When using this product

- wash hands after use with cool water
- avoid contact with eyes or mucous membranes
- do not bandage

Stop use and ask a doctor if

- condition worsens or symptoms persists for more than 7 days
- symptoms clear up and occur again within a few days
- excessive skin irritation occurs

PREGNANCY OR BREAST FEEDING

If pregnant or breast-feeding, ask a health profiessional before use.

Keep out of reach of children to avoid accidental poisoning. If swallowed, induce vomiting and call a physician or contact a Poison Control Center right away.

Directions

- use only as directed
- Adults and children over 12 years: rub a thin film over affected areas not more than 4 times daily: message not necessary.
- Children 12 years or younger: do not use.

INACTIVE INGREDIENT

Inactive ingredients Camphor, carbomer 940, D&C yellow #10, FD&C yellow #5, glycerin, isopropyl myristate, methyl salicylate, methylchloroisothiazolinone, methlylisothiazolinone, polysorbate 20, propylene glycol, triethanolamine, water.

QUESTIONS

Questions? Call 1-800-560-5223 M-F 9 AM to 4 PM Eastern